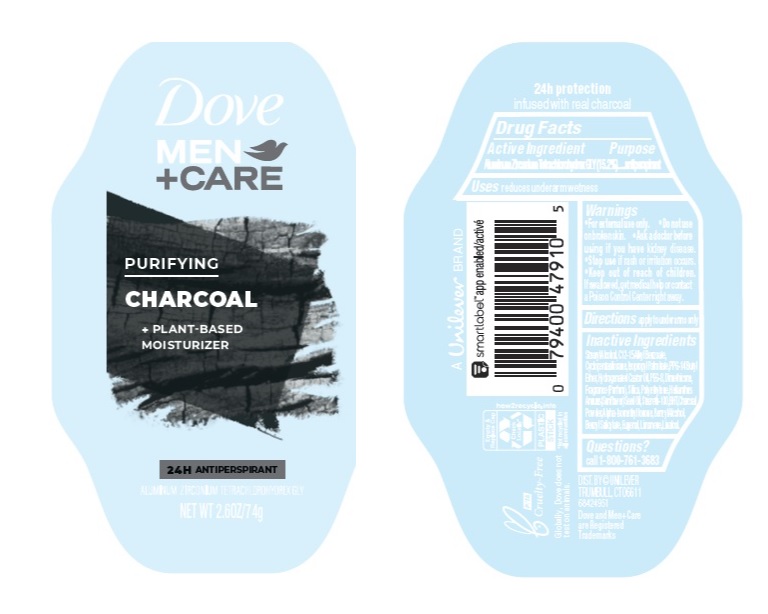 DRUG LABEL: Dove
NDC: 64942-1783 | Form: STICK
Manufacturer: Conopco Inc. d/b/a/ Unilever
Category: otc | Type: HUMAN OTC DRUG LABEL
Date: 20241110

ACTIVE INGREDIENTS: ALUMINUM ZIRCONIUM TETRACHLOROHYDREX GLY 15.2 g/100 g
INACTIVE INGREDIENTS: CITRAL; .BETA.-CITRONELLOL, (R)-; HIGH DENSITY POLYETHYLENE; CYCLOMETHICONE 5; HYDROGENATED CASTOR OIL; BUTYLATED HYDROXYTOLUENE; PPG-14 BUTYL ETHER; STEARYL ALCOHOL; SUNFLOWER OIL; SILICON DIOXIDE; ALKYL (C12-15) BENZOATE; DIMETHICONE; STEARETH-100; POLYETHYLENE GLYCOL 400; ISOPROPYL PALMITATE; GERANIOL; COUMARIN; LIMONENE, (+)-; LINALOOL, (+/-)-

Dove Men plus Care Purifying Charcoal 24H Antiperspirant

DOVE MEN PLUS CARE PURIFYING CHARCOAL 24H ANTIPERSPIRANT - aluminum zirconium tetrachlorohydrex gly stick

Dove Men plus Care Purifying Charcoal 24H Antiperspirant

Drug Facts

Active ingredient

Aluminum Zirconium Tetrachlorohydrex GLY (15.2 %)

Purpose

antiperspirant

Uses

reduces underarm wetness

Warnings

• For externaluse only.
• Do not use on broken skin .
• Ask a doctor before use if you have kidney disease.
• Stop use if rash or irritation occurs.

• Keep out of reach of children.

If swallowed, get medical help or contact a Poison Control Center right away.

Directions

apply to underarms only

Inactive ingredients

Stearyl Alcohol, C12-15 Alkyl Benzoate, Cyclopentasiloxane, Isopropyl Palmitate, PPG-14 Butyl Ether, Hydrogenated Castor Oil, PEG-8, Dimethicone, Fragrance (Parfum), Silica, Polyethylene, Helianthus Annuus (Sunflower) Seed Oil, Steareth-100, BHT, Citral, Citronellol, Coumarin, Geraniol, Limonene, Linalool.

Questions?

Call 1-800-761-3683